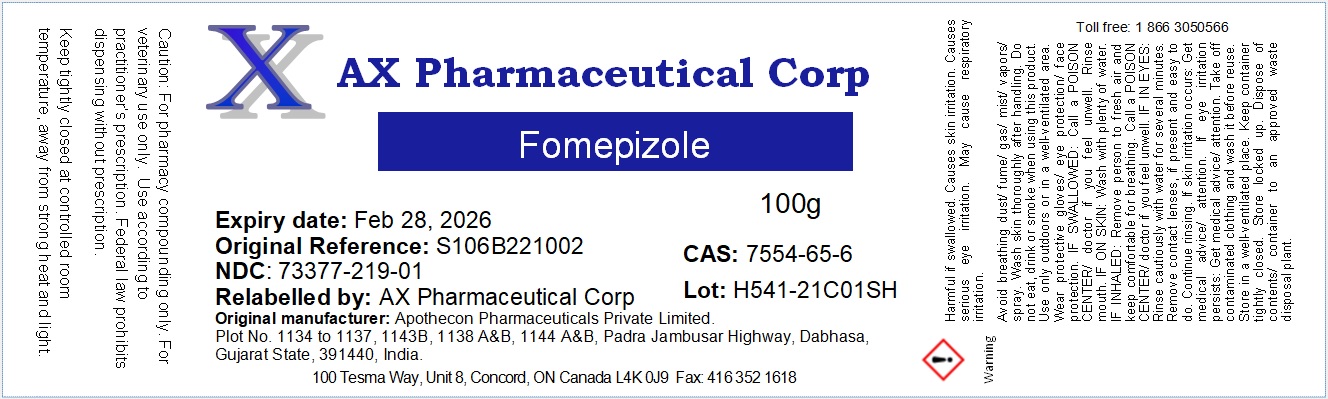 DRUG LABEL: Fomepizole
NDC: 73377-219 | Form: LIQUID
Manufacturer: AX Pharmaceutical Corp
Category: other | Type: BULK INGREDIENT - ANIMAL DRUG
Date: 20230127

ACTIVE INGREDIENTS: FOMEPIZOLE 1 g/1 g

Fomepizole